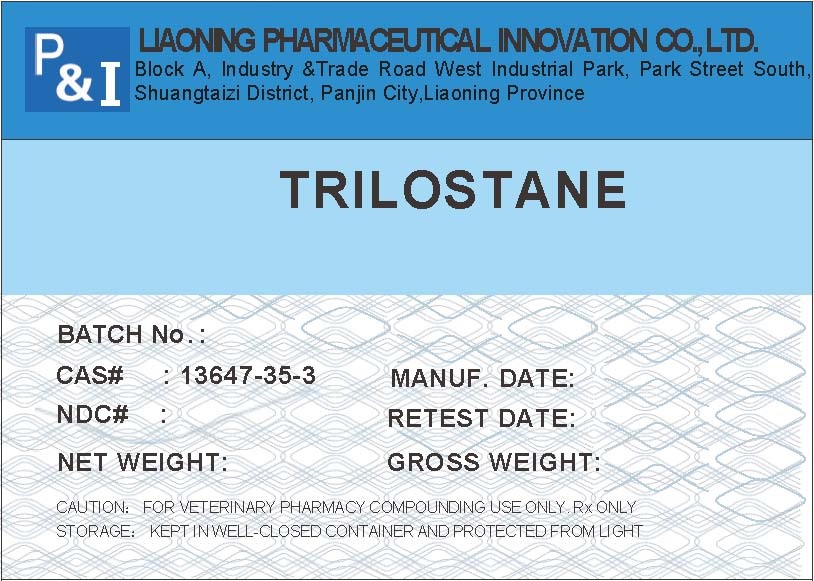 DRUG LABEL: Trilostane
NDC: 86212-001 | Form: POWDER
Manufacturer: Liaoning Pharmaceutical Innovation Co., Ltd.
Category: other | Type: BULK INGREDIENT - ANIMAL DRUG
Date: 20251208

ACTIVE INGREDIENTS: TRILOSTANE 1 kg/1 kg

Trilostane

Trilostane_label_20241115.jpg